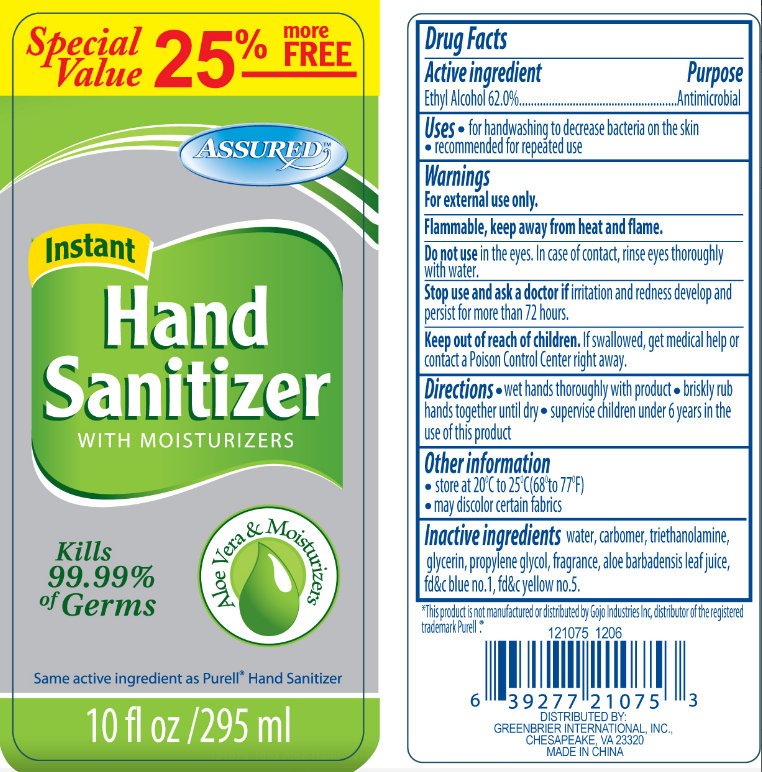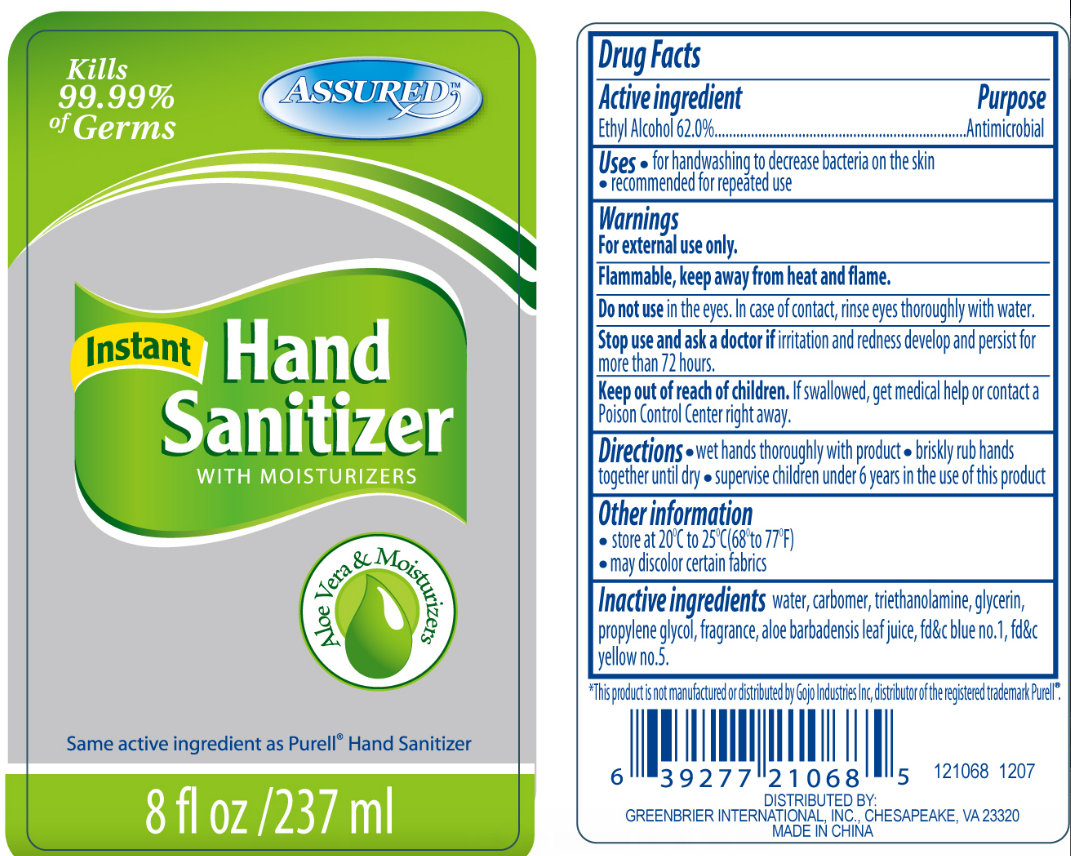 DRUG LABEL: ASSURED Instant Hand Sanitizer WITH MOISTURIZERS Aloe Vera and Moisturizers
NDC: 33992-1061 | Form: GEL
Manufacturer: Greenbrier International, Inc.
Category: otc | Type: HUMAN OTC DRUG LABEL
Date: 20120509

ACTIVE INGREDIENTS: ALCOHOL 62 mL/100 mL
INACTIVE INGREDIENTS: WATER; TROLAMINE; GLYCERIN; PROPYLENE GLYCOL; ALOE VERA LEAF; FD&C BLUE NO. 1; FD&C YELLOW NO. 5

ASSURED Instant Hand Sanitizer WITH MOISTURIZERS Aloe Vera and Moisturizers

Active Ingredient

Ethyl Alcohol 62.0%

Purpose

Antimicrobial

Uses

- for handwashing to decrease bacteria on the skin
- recommended for repeated use

Warnings

For external use only.

Flammable, keep away from heat and flame.

Do not use

in the eyes. In case of contact, rinse eyes thoroughly with water.

Stop use and ask a doctor if

irritation and redness develop and persist for more than 72 hours.

Keep out of reach of children

If swallowed, get medical help or contact a Poison Control Center right away.

Directions

- wet hands thoroughly with product
- briskly rub hand until dry
- supervise children under 6 years in the use of this product

Other Information

- store at 20 degrees C to 25 degrees C (68 degrees to 77 degrees F)
- may discolor certain fabrics

Inactive Ingredients

water, carbomer, triethanolamine , glycerin, propylene glycol, fragrance, aloe barbadensis leaf juice, fd and c blue no.,1, fd and c yellow no. 5

This product is not manufactured or distributed by Gojo Industruies Inc, distributor of the registered trademark Purell

Distributed By: GREENBRIAR INTERNATIONAL, INC.,

CHESAPEAKE, VA 23320

MADE IN CHINA

PACKAGE LABEL

ASSURED

Kills 99.99 percent of Germs

Instant Hand Sanitizer

with Moisturizers

Aloe Vera and Moisturizers

Same active ingredient as Purell Hand Sanitizer